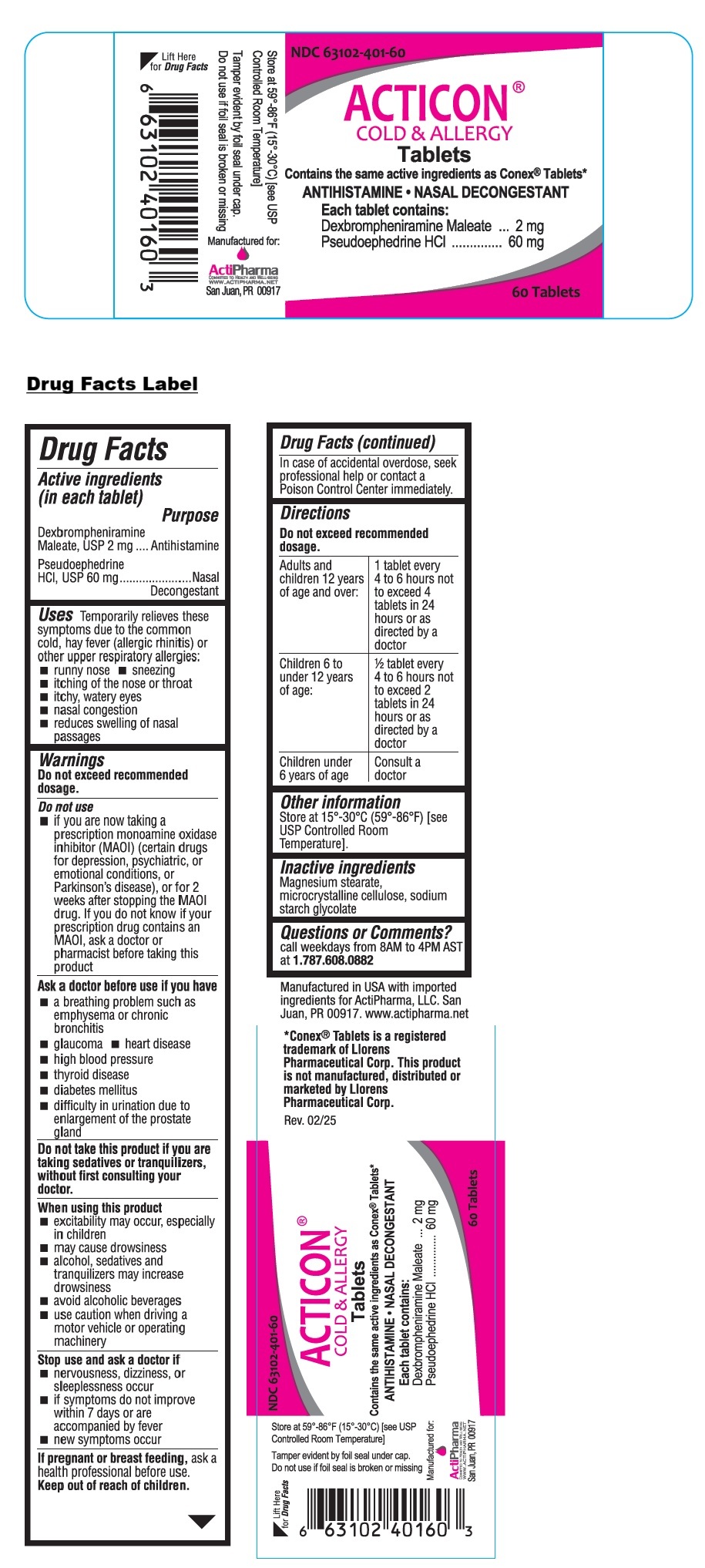 DRUG LABEL: ACTICON
NDC: 63102-401 | Form: TABLET
Manufacturer: ACTIPHARMA, LLC
Category: otc | Type: HUMAN OTC DRUG LABEL
Date: 20250708

ACTIVE INGREDIENTS: DEXBROMPHENIRAMINE MALEATE 2 mg/1 1; PSEUDOEPHEDRINE HYDROCHLORIDE 60 mg/1 1
INACTIVE INGREDIENTS: MAGNESIUM STEARATE; MICROCRYSTALLINE CELLULOSE; SODIUM STARCH GLYCOLATE TYPE A

ACTICON® COLD & ALLERGY Tablets

Active ingredients (in each tablet)

Dexbrompheniramine Maleate, USP 2 mg
Pseudoephedrine HCl, USP 60 mg

Purpose

Antihistamine
Nasal Decongestant

Uses

Temporarily relieves these symptoms due to the common cold, hay fever (allergic rhinitis) or other upper respiratory allergies:
• runny nose • sneezing
• itching of the nose or throat
• itchy, watery eyes
• nasal congestion
• reduces swelling of nasal passages

Warnings

Do not exceed recommended dosage.

Do not use
• if you are now taking a prescription monoamine oxidase inhibitor (MAOI) (certain drugs for depression, psychiatric, or emotional conditions, or Parkinson’s disease), or for 2 weeks after stopping the MAOI drug. If you do not know if your prescription drug contains an MAOI, ask a doctor or pharmacist before taking this product

Ask a doctor before use if you have
• a breathing problem such as emphysema or chronic bronchitis
• glaucoma • heart disease
• high blood pressure
• thyroid disease
• diabetes mellitus
• difficulty in urination due to enlargement of the prostate gland

Do not take this product if you are taking sedatives or tranquilizers, without first consulting your doctor.

When using this product
• excitability may occur, especially in children
• may cause drowsiness
• alcohol, sedatives and tranquilizers may increase drowsiness
• avoid alcoholic beverages
• use caution when driving a motor vehicle or operating machinery

Stop use and ask a doctor if
• nervousness, dizziness, or sleeplessness occur
• if symptoms do not improve within 7 days or are accompanied by fever
• new symptoms occur

If pregnant or breast feeding, ask a health professional before use.

Keep out of reach of children. In case of accidental overdose, seek professional help or contact a Poison Control Center immediately.

Directions

Do not exceed recommended dosage.

Adults and children 12 years of age and over: | 1 tablet every 4 to 6 hours not to exceed 4 tablets in 24 hours or as directed by a doctor
Children 6 to under 12 years of age: | 1/2 tablet every 4 to 6 hours not to exceed 2 tablets in 24 hours or as directed by a doctor
Children under 6 years of age | Consult a doctor

Other information

Store at 15°-30°C (59°-86°F) [see USP Controlled Room Temperature].

Inactive ingredients

Magnesium stearate, microcrystalline cellulose, sodium starch glycolate

Questions or Comments?

call weekdays from 8AM to 4PM AST at 1.787.608.0882

Contains the same active ingredients as Conex® Tablets*

Manufactured in USA with imported ingredients for ActiPharma, LLC. San Juan, PR 00917. www.actipharma.net

*Conex® Tablets is a registered trademark of Llorens Pharmaceutical Corp. This product is not manufactured, distributed or marketed by Llorens Pharmaceutical Corp.

Tamper evident by foil seal under cap.
Do not use if foil seal is broken or missing.

Manufactured for:
ActiPharma
COMMITTED TO HEALTH AND WELL-BEING
WWW.ACTIPHARMA.NET
San Juan, PR 00917